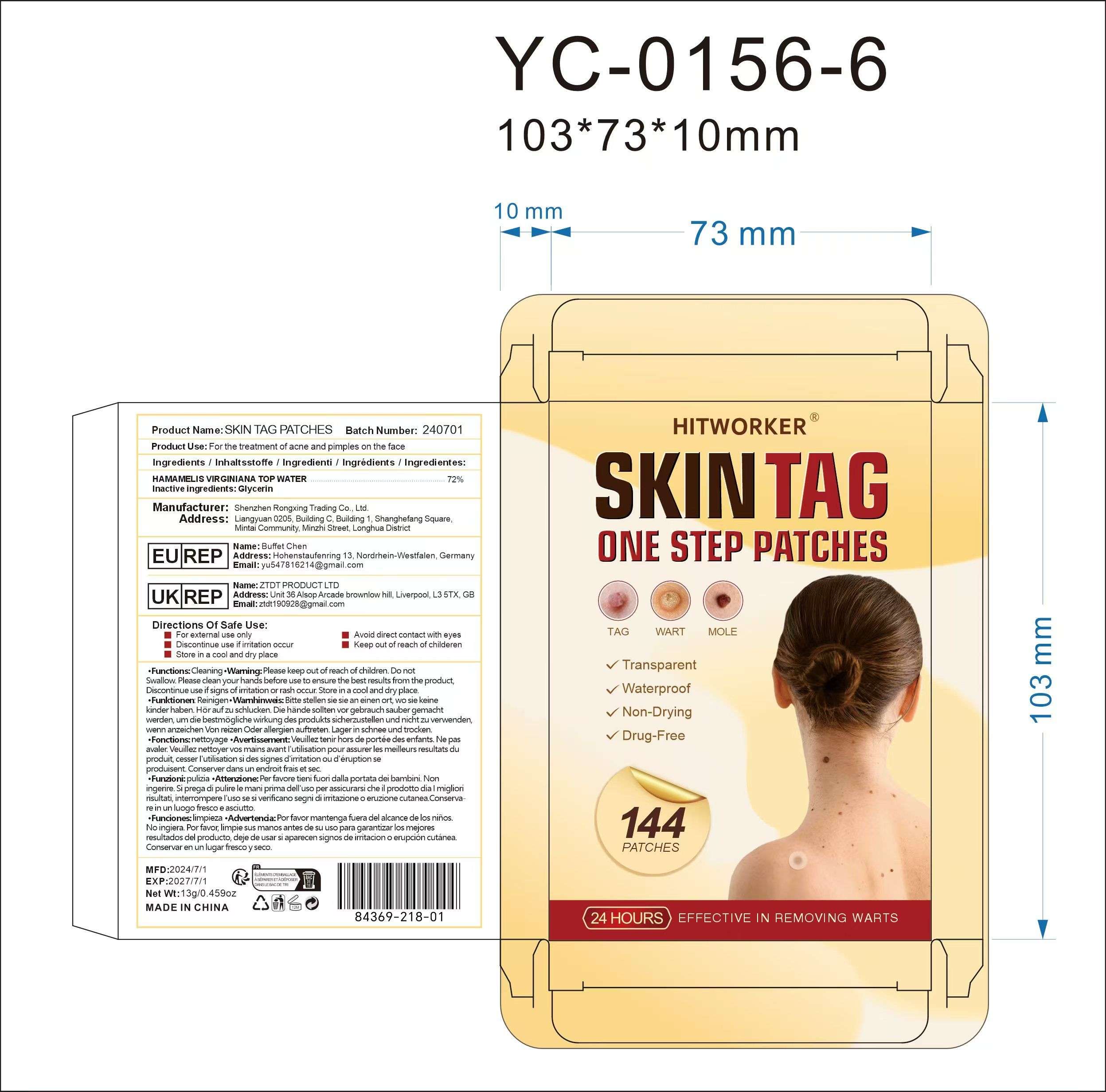 DRUG LABEL: Skin tag patches
NDC: 84369-218 | Form: PATCH
Manufacturer: Shenzhen Rongxing Trading Co., Ltd.
Category: otc | Type: HUMAN OTC DRUG LABEL
Date: 20241108

ACTIVE INGREDIENTS: HAMAMELIS VIRGINIANA TOP WATER 72 g/100 g
INACTIVE INGREDIENTS: GLYCERIN

Ingredients / Inhaltsstoffe / Ingredienti / Ingredients / Ingredientes:

HAMAMELIS VIRGINIANA TOP WATER 72%

Inactive ingredients:

GLYCERIN

Product Use:

For the treatment of acne and pimples on the face

Directions Of safe Use:

For external use only

Avoid direct contact with eyes

Discontinue use if irritation occur

Keep out of reach of childeren

Store in a cool and dry place

Warning:

Please keep outof reach of children.Do not

Swallow.Please clean yourhandsbefore use to ensure the best results from the product

Discontinue use if signs of irritation orrash occur Store in a cool and dry place.

Dosage and administration:

For external use only.

Do not use:

Please keep outof reach of children.Do not

Swallow.Please clean yourhandsbefore use to ensure the best results from the product

Discontinue use if signs of irritation orrash occur Store in a cool and dry place.

When using section:

Please keep outof reach of children.Do not

Swallow.Please clean yourhandsbefore use to ensure the best results from the product

Discontinue use if signs of irritation orrash occur Store in a cool and dry place.

stop use:

Please keep outof reach of children.Do not

Swallow.Please clean yourhandsbefore use to ensure the best results from the product

Discontinue use if signs of irritation orrash occur Store in a cool and dry place.

Keep out of reach of children:

Please keep outof reach of children.Do not

Swallow.Please clean yourhandsbefore use to ensure the best results from the product

Discontinue use if signs of irritation orrash occur Store in a cool and dry place.